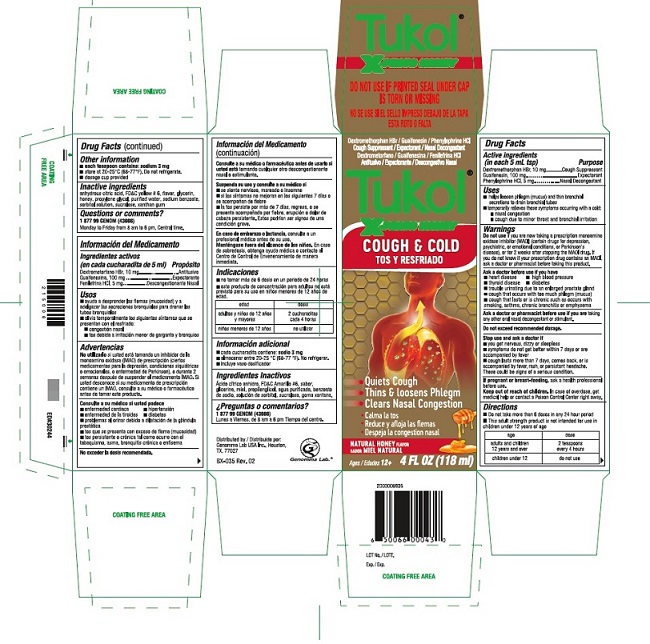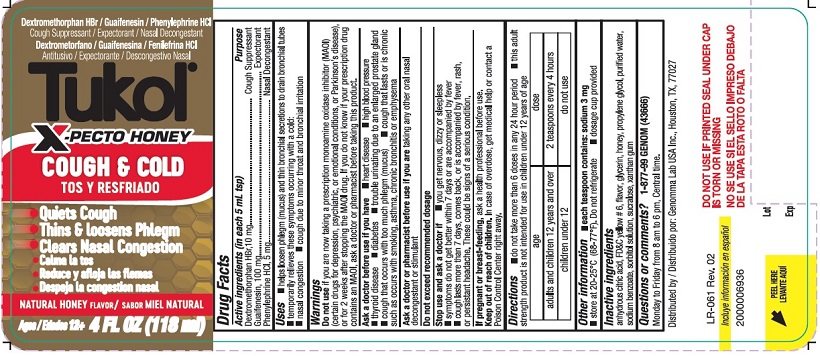 DRUG LABEL: Tukol X-Pecto Miel 
NDC: 50066-533 | Form: LIQUID
Manufacturer: Genomma Lab USA, Inc.
Category: otc | Type: HUMAN OTC DRUG LABEL
Date: 20241220

ACTIVE INGREDIENTS: DEXTROMETHORPHAN HYDROBROMIDE 10 mg/5 mL; GUAIFENESIN 100 mg/5 mL; PHENYLEPHRINE HYDROCHLORIDE 5 mg/5 mL
INACTIVE INGREDIENTS: ANHYDROUS CITRIC ACID; FD&C YELLOW NO. 6; GLYCERIN; HONEY; PROPYLENE GLYCOL; WATER; SODIUM BENZOATE; SORBITOL; SUCRALOSE; XANTHAN GUM

Tukol® X-PECTO MIEL Cough & Cold 533

DRUG FACTSActive ingredients (in each 5 mL tsp)

Dextromethorphan HBr, USP 10 mg
Guaifenesin, USP 100 mg
Phenylephrine HCL, USP 5 mg

Purposes

Cough Suppressant
Expectorant
Nasal Decongestant

Keep out of reach of children.
In case of overdose, get medical help or contact a Poison Control Center right away.

Uses

- help loosen phlegm (mucus) and thin bronchial secretions to drain bronchial tubes
- temporarily relieves these symptoms occurring with a cold

• nasal congestion

• cough due to minor throat and bronchial irritation

Warnings

Do not use if you are now taking a prescription monoamine oxidase inhibitor (MAOI) (certain drugs for depression, psychiatric, or emotional conditions, or Parkinson's disease), or for 2 weeks after stopping the MAOI drug. If you do not know if your prescription drug contains an MAOI, ask a doctor or pharmacist before taking this product.

Ask a doctor or pharmacist before use if you are taking any other oral nasal decongestant or stimulant.
When using this product do not use more than directed.

Ask a doctor before use if you have

- heart disease
- high blood pressure
- thyroid disease
- diabetes
- trouble urinating due to an enlarged prostate gland
- cough that occurs with too much phlegm (mucus)
- cough that lasts or is chronic such as occurs with smoking, asthma, chronic bronchitis or emphysema

Stop use and ask a doctor if

- you get nervous, dizzy or sleepless
- symptoms do not get better within 7 days, or are accompanied by fever
- cough lasts more than 7 days, comes back, or is accompanied by fever, rash, or persistent headache.

These could be signs of a serious condition.

If pregnant or breast-feeding

ask a health professional before use.

Directions

- Do not take more than 6 doses in any 24 hour period
- This adult strength product is not intended for use in children under 12 years of age

Age - adults and children 12 years and over Dose - 2 teaspoons every 4 hours
Age - children under 12 Dose - do not use

Other information

- each teaspoon contains: sodium 3 mg
- store at 20‐25 ° C (68‐77 ° F). Do not refrigerate.
- dosage cup provided

Inactive ingredients

anhydrous citric acid, FD and C yellow # 6, flavor, glycerin, honey, propylene glycol, purified water, sodium benzoate, sorbitol solution, sucralose, xanthan gum

Questions or comments?

1 877 99 GENOM (43666)

Monday to Friday from 8 am to 6 pm, Central time.

Tukol X-PECTO MIEL Cough & Cold product label

Tukol®

X-PECTO MIEL

DO NOT USE IF PRINTED SEAL UNDER CAP IS TORN OR MISSING

Dextromethorphan HBr / Guaifenesin / Phenylephrine HCL

Cough Suppressant / Expectorant / Nasal Decongestant

Tukol®

X-PECTO MIEL

Cough & Cold

- Quiets Cough
- Thins & loosens Phlegm
- Clears Nasal Congestion

NATURAL HONEY FLAFOR
Ages / 12+ 4 FL OZ (118 ml)

2000006935

6 50066 00042 0

LOT no.

Exp.

Distributed by Genomma Lab USA Inc.

Houston TX, 77027

BX-035 Rev. 02

Genomma Lab.®

rege